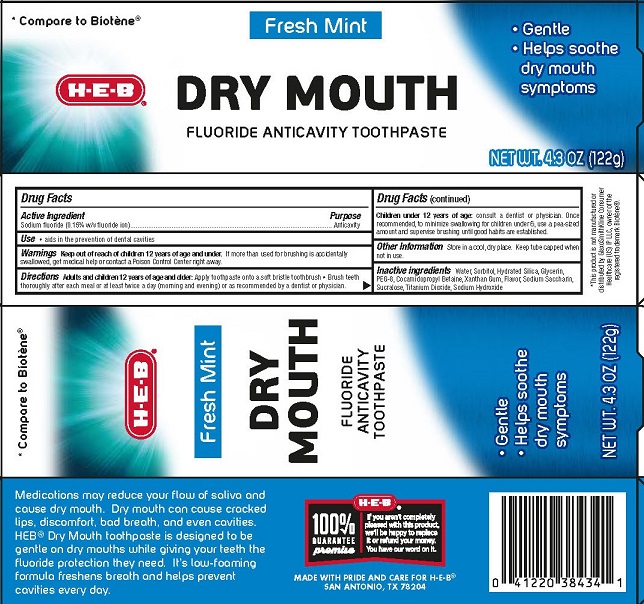 DRUG LABEL: HEB
NDC: 37808-331 | Form: PASTE, DENTIFRICE
Manufacturer: HEB
Category: otc | Type: HUMAN OTC DRUG LABEL
Date: 20250808

ACTIVE INGREDIENTS: SODIUM FLUORIDE 0.15 g/100 g
INACTIVE INGREDIENTS: GLYCERIN; SACCHARIN SODIUM; WATER; SODIUM HYDROXIDE; TITANIUM DIOXIDE; SUCRALOSE; HYDRATED SILICA; COCAMIDOPROPYL BETAINE; SORBITOL; POLYETHYLENE GLYCOL, UNSPECIFIED; XANTHAN GUM

5820020 HEB Dry Mouth

Active ingredient

Sodium Fluoride (0.15% w/v fluoride ion)

Purpose

Anticavity

Use

- aids in the prevention of dental cavities

Warnings

Keep out of reach of children 12 years of age and under. If more than used for brushing is accidently swallowed, get medical help or contact a Poison Control Center right away.

Directions

Adults and children 12 years of age and older: Apply onto a soft bristle toothbrush.

- Brush teeth thoroughly for at least one minute, preferably after each meal or at least twice a day (morning and evening) or as recommended by a dentist or physician.

Children under 12 years of age: consult a dentist or physician. Once recommended, to minimize swallowing for children under 6,use a pea sized amount and supervise brushing until good habits are established.

Other information

Store in a cool dry place. Keep tube capped when not in use.

Inactive ingredients

Water, Sorbitol, Hydrated Silica, Glycerin, PEG-8, Cocamidopropyl Betaine, Xanthan Gum, Flavor, Sodium Saccharin, Sucralose, Titanium Dioxide, Sodium Hydroxide.

MADE WITH PRIDE AND CARE FOR H-E-B®

SAN ANTONIO, TX 78204

PACKAGE LABEL

H-E-B®

DRY MOUTH

FLUORIDE ANTICAVITY TOOTHPASTE

Fresh Mint

NET WT. 4.3 OZ (122g)